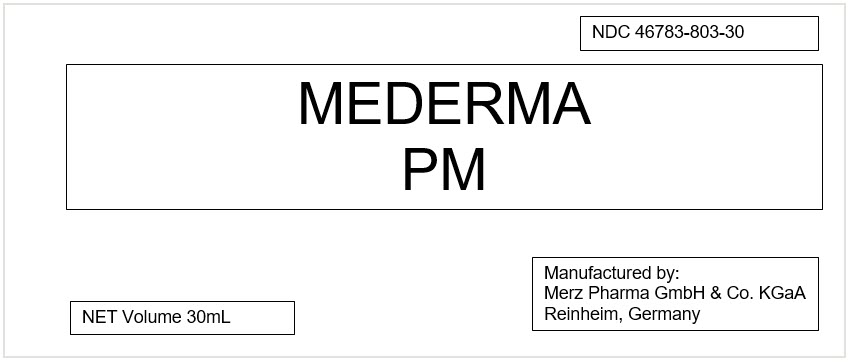 DRUG LABEL: Mederma PM
NDC: 46783-803 | Form: CREAM
Manufacturer: Merz North America
Category: otc | Type: HUMAN OTC DRUG LABEL
Date: 20240314

ACTIVE INGREDIENTS: DIMETHICONE 20 mg/1 mL
INACTIVE INGREDIENTS: WATER; CETOSTEARYL ALCOHOL; GLYCERIN; ALKYL (C12-15) BENZOATE; DICAPRYLYL CARBONATE; PENTYLENE GLYCOL; CYCLOMETHICONE; ARACHIDYL ALCOHOL; ALCOHOL; DOCOSANOL; ARACHIDYL GLUCOSIDE; ONION; PREZATIDE COPPER; ALOE VERA LEAF; CETEARYL GLUCOSIDE; .ALPHA.-TOCOPHEROL ACETATE; HYDROXYETHYL ACRYLATE/SODIUM ACRYLOYLDIMETHYL TAURATE COPOLYMER (100000 MPA.S AT 1.5%); HYDROXYETHYL CELLULOSE (2000 MPA.S AT 1%); SOY PROTEIN; GLYCINE; PANTHENOL; BOVINE TYPE I COLLAGEN; POLYETHYLENE GLYCOL 400; ARGININE HYDROCHLORIDE; LEUCINE; LYSINE HYDROCHLORIDE; ALANINE; SODIUM LACTATE; ASPARTIC ACID; DEXTROSE, UNSPECIFIED FORM; GLUTAMIC ACID; ISOPROPYL ALCOHOL; MANNITOL; SORBITOL; TROMETHAMINE; VALINE; HISTIDINE MONOHYDROCHLORIDE; ISOLEUCINE; PHENYLALANINE; TYROSINE; POTASSIUM SORBATE; SODIUM BENZOATE; CITRIC ACID MONOHYDRATE; SODIUM HYDROXIDE

Mederma PM

PRINCIPAL DISPLAY PANEL - 30 mL Tube Box Label

NDC 46783-803-30

MEDERMA
PM

NET Volume 30mL

Manufactured by:
Merz Pharma GmbH & Co. KGaA
Reinheim, Germany